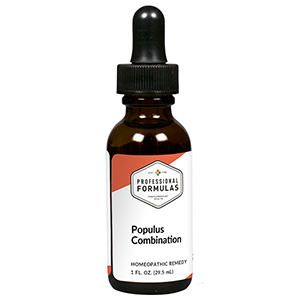 DRUG LABEL: Populus Combination
NDC: 63083-9236 | Form: LIQUID
Manufacturer: Professional Complementary Health Formulas
Category: homeopathic | Type: HUMAN OTC DRUG LABEL
Date: 20190815

ACTIVE INGREDIENTS: POPULUS TREMULOIDES BARK 1 [hp_X]/29.5 mL; SAW PALMETTO 1 [hp_X]/29.5 mL; APIS MELLIFERA 3 [hp_X]/29.5 mL; BAPTISIA TINCTORIA WHOLE 3 [hp_X]/29.5 mL; CAMPHOR (NATURAL) 3 [hp_X]/29.5 mL; CAPSICUM 3 [hp_X]/29.5 mL; PIPER CUBEBA FRUIT 3 [hp_X]/29.5 mL; EQUISETUM HYEMALE WHOLE 3 [hp_X]/29.5 mL; ONONIS REPENS WHOLE 3 [hp_X]/29.5 mL; RUBIA TINCTORUM ROOT 3 [hp_X]/29.5 mL; SCROPHULARIA NODOSA WHOLE 3 [hp_X]/29.5 mL; SOLIDAGO VIRGAUREA FLOWERING TOP 3 [hp_X]/29.5 mL; URTICA URENS WHOLE 3 [hp_X]/29.5 mL; ARCTOSTAPHYLOS TOMENTOSA WHOLE 3 [hp_X]/29.5 mL; PETROSELINUM CRISPUM ROOT 4 [hp_X]/29.5 mL; BERBERIS VULGARIS ROOT BARK 5 [hp_X]/29.5 mL; LYTTA VESICATORIA 5 [hp_X]/29.5 mL; AGATHOSMA BETULINA LEAF 6 [hp_X]/29.5 mL; WOOD CREOSOTE 6 [hp_X]/29.5 mL; DRIMIA MARITIMA BULB 6 [hp_X]/29.5 mL; TURPENTINE OIL 6 [hp_X]/29.5 mL; MERCURIC CHLORIDE 12 [hp_X]/29.5 mL
INACTIVE INGREDIENTS: ALCOHOL; WATER

R236

ACTIVE INGREDIENTS

Populus tremuloides 1X
Sabal serrulata 1X
Apis mellifica 3X
Baptisia tinctoria 3X
Camphora 3X
Capsicum annuum 3X
Cubeba officinalis 3X
Equisetum hyemale 3X
Ononis spinosa 3X
Rubia tinctorum 3X
Scrophularia nodosa 3X
Solidago virgaurea 3X
Urtica urens 3X
Uva-ursi 3X
Petroselinum sativum 4X
Berberis vulgaris 5X
Cantharis 5X
Barosma crenata 6X
Kreosotum 6X
Scilla maritima 6X
Terebinthina 6X
Mercurius corrosivus 12X

QUESTIONS

Professional Formulas

PO Box 2034 Lake Oswego, OR 97035

INDICATIONS

For the temporary relief of constipation, diarrhea, or frequent urination.*

PURPOSE

*Claims based on traditional homeopathic practice, not accepted medical evidence. Not FDA evaluated.

WARNINGS

Consult a doctor if condition worsens or if symptoms persist. Keep out of the reach of children. In case of overdose, get medical help or contact a poison control center right away. If pregnant or breastfeeding, ask a healthcare professional before use.

Keep out of the reach of children.

PREGNANCY OR BREAST FEEDING

If pregnant or breastfeeding, ask a healthcare professional before use.

DIRECTIONS

Place drops under tongue 30 minutes before/after meals. Adults and children 12 years and over: Take 10 drops up to 3 times per day. Consult a physician for use in children under 12 years of age.

OTHER INFORMATION

Tamper resistant. If seal is broken, do not use. After opening, close container tightly and store at room temperature away from heat.

INACTIVE INGREDIENTS

40% ethanol, purified water.

LABEL

Est 1985

Professional Formulas

Complementary Health

Populus Combination

Homeopathic Remedy

1 FL. OZ. (29.5 mL)